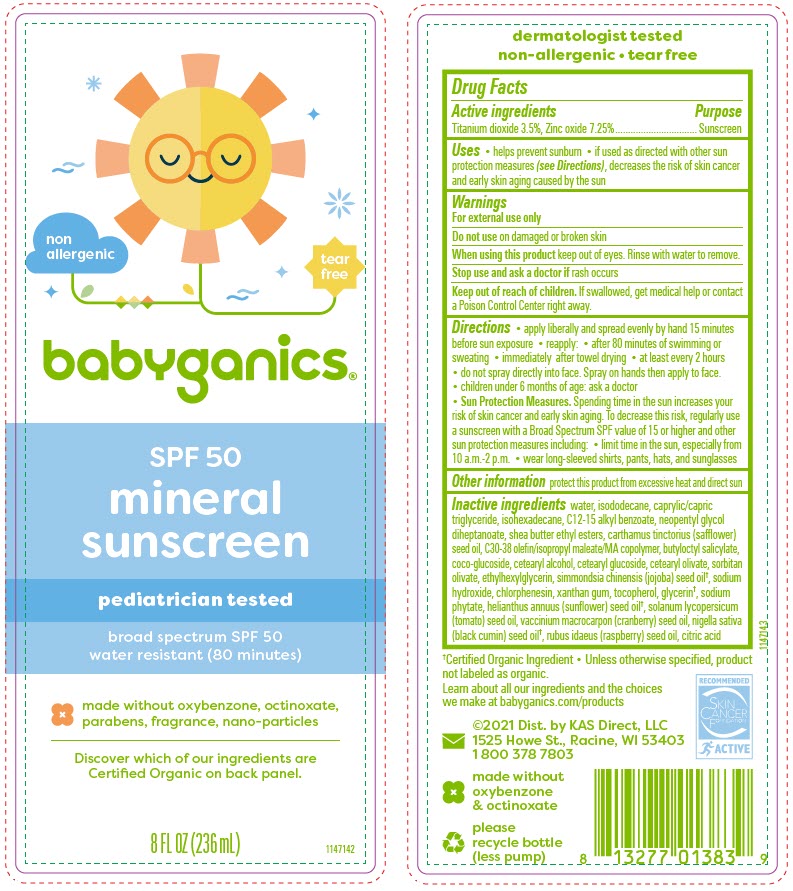 DRUG LABEL: SPF50 Plus Mineral Sunscreen
NDC: 59062-2210 | Form: SPRAY
Manufacturer: KAS Direct LLC dba BabyGanics
Category: otc | Type: HUMAN OTC DRUG LABEL
Date: 20241017

ACTIVE INGREDIENTS: ZINC OXIDE 7.25 g/100 mL; TITANIUM DIOXIDE 3.5 g/100 mL
INACTIVE INGREDIENTS: WATER; ISODODECANE; MEDIUM-CHAIN TRIGLYCERIDES; ISOHEXADECANE; ALKYL (C12-15) BENZOATE; NEOPENTYL GLYCOL DIHEPTANOATE; SHEA BUTTER ETHYL ESTERS; SAFFLOWER OIL; DIDECYLDIMONIUM CHLORIDE; BUTYLOCTYL SALICYLATE; COCO GLUCOSIDE; CETOSTEARYL ALCOHOL; CETEARYL GLUCOSIDE; CETEARYL OLIVATE; SORBITAN OLIVATE; ETHYLHEXYLGLYCERIN; JOJOBA OIL; SODIUM HYDROXIDE; CHLORPHENESIN; XANTHAN GUM; TOCOPHEROL; GLYCERIN; PHYTATE SODIUM; SUNFLOWER SEED; TOMATO SEED OIL; CRANBERRY SEED; NIGELLA SATIVA SEED OIL; RUBUS IDAEUS SEED; CITRIC ACID MONOHYDRATE

SPF50+ Mineral Sunscreen Spray

Drug Facts

Active ingredients

Titanium dioxide 3.5%, Zinc oxide 7.25%

Purpose

Sunscreen

Uses

- helps prevent sunburn
- if used as directed with other sun protection measures (see Directions) , decreases the risk of skin cancer and early skin aging caused by the sun

Warnings

For external use only

Do not useon damaged or broken skin

WHEN USING

When using this productkeep out of eyes. Rinse with water to remove.

Stop use and ask a doctor ifrash occurs

Keep out of reach of children.If swallowed, get medical help or contact a Poison Control Center right away.

Directions

- apply liberally and spread evenly by hand 15 minutes before sun exposure
- reapply:
  - after 80 minutes of swimming or sweating
  - immediately after towel drying
  - at least every 2 hours
- do not spray directly into face. Spray on hands then apply to face.
- children under 6 months of age: ask a doctor
- Sun Protection Measures.Spending time in the sun increases your risk of skin cancer and early skin aging. To decrease this risk, regularly use a sunscreen with a Broad Spectrum SPF value of 15 or higher and other sun protection measures including:
  - limit time in the sun, especially from 10 a.m.-2 p.m.
  - wear long-sleeved shirts, pants, hats, and sunglasses

Other information

protect this product from excessive heat and direct sun

Inactive ingredients

water, isododecane, caprylic/capric triglyceride, isohexadecane, C12-15 alkyl benzoate, neopentyl glycol diheptanoate, shea butter ethyl esters, carthamus tinctorius (safflower) seed oil, C30-38 olefin/isopropyl maleate/MA copolymer, butyloctyl salicylate, coco-glucoside, cetearyl alcohol, cetearyl glucoside, cetearyl olivate, sorbitan olivate, ethylhexylglycerin, simmondsia chinensis (jojoba) seed oil [Certified Organic Ingredient • Unless otherwise specified, product not labeled as organic.] , sodium hydroxide, chlorphenesin, xanthan gum, tocopherol, glycerin , sodium phytate, helianthus annuus (sunflower) seed oil , solanum lycopersicum (tomato) seed oil, vaccinium macrocarpon (cranberry) seed oil, nigella sativa (black cumin) seed oil , rubus idaeus (raspberry) seed oil, citric acid

Dist. by KAS Direct, LLC
1525 Howe St., Racine, WI 53403

PRINCIPAL DISPLAY PANEL - 236 mL Bottle Label

non
allergenic

tear
free

babyganics®

SPF 50
mineral
sunscreen

pediatrician tested

broad spectrum SPF 50
water resistant (80 minutes)

made without oxybenzone, octinoxate,
parabens, fragrance, nano-particles

Discover which of our ingredients are
Certified Organic on back panel.

8 FL OZ (236 mL)

1147142